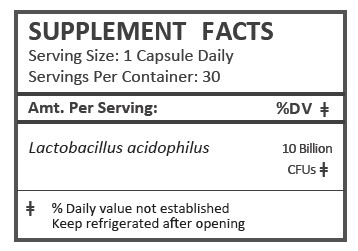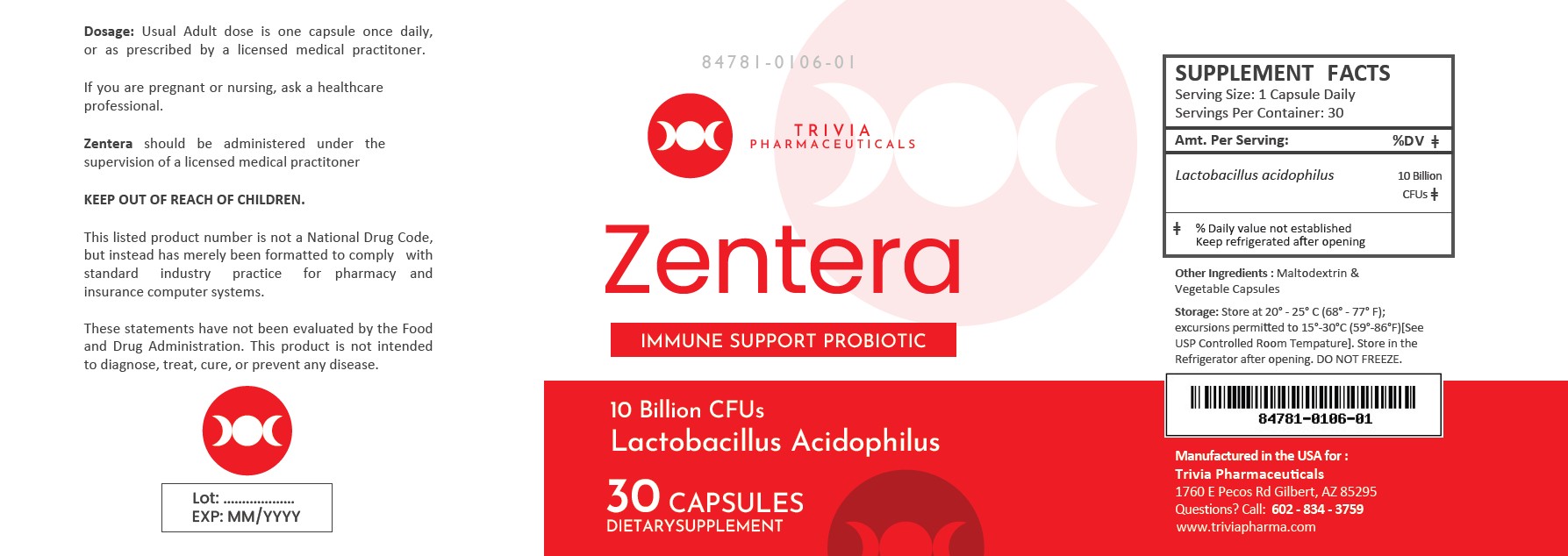 DRUG LABEL: ZENTERA
NDC: 84781-106 | Form: CAPSULE
Manufacturer: Trivia Pharmaceuticals, LLC
Category: other | Type: DIETARY SUPPLEMENT
Date: 20250523

ACTIVE INGREDIENTS: LACTOBACILLUS ACIDOPHILUS 10000000000 [CFU]/1 1
INACTIVE INGREDIENTS: MALTODEXTRIN

Zentera Probiotic Capsules
Dietary Supplement

HEALTH CLAIM:

Zentera Probiotic Capsules Dietary Supplement
Dispensed by Prescription

Other Ingredients: Maltodextrin, Vegetable Capsules

DESCRIPTION:

Zentera Probiotic Capsules are an orally administered prescription probiotic formulation for the clinical dietary management of suboptimal nutritional status in patients where advanced supplementation is required and nutritional supplementation in physiologically stressful conditions for maintenance of good health is needed.

Zentera Probiotic Capsules should be administered under the supervision of a licensed medical practitioner.

This listed product is not a National Drug Code, but instead has merely been formatted to comply with standard industry practice for pharmacy and insurance computer systems.

WARNINGS AND PRECAUTIONS:

This product is contraindicated in patients with a known hypersensitivity to any of the ingredients.

GutVite should only be used under the direction and supervision of a licensed medical practitioner. Use with caution in patients that may have a medical condition, are pregnant, lactating, trying to conceive, under the age of 18, or taking medications.

DOSAGE AND ADMINISTRATION:

Usual adult dose is 1 capsule by mouth daily with or without food.

HOW SUPPLIED:

Zentera Probiotic Capsules are supplied as clear capsules dispensed in plastic bottles of 30 ct.

84781-100-02

Reserved for Professional Recommendation

All prescriptions using this product shall be pursuant to state statutes as applicable. This is not an Orange Book product. This product may be administered only under a physician’s supervision. There are no implied or explicit claims on therapeutic equivalence.

Manufactured for:
Trivia Pharmaceuticals

Gilbert, AZ

STORAGE:

Store at 20° - 25° C (68° - 77° F); excursions permitted to 15°-30°C (59°-86°F)[See USP Controlled Room Tempature].

Store in the Refrigerator after opening. DO NOT FREEZE.